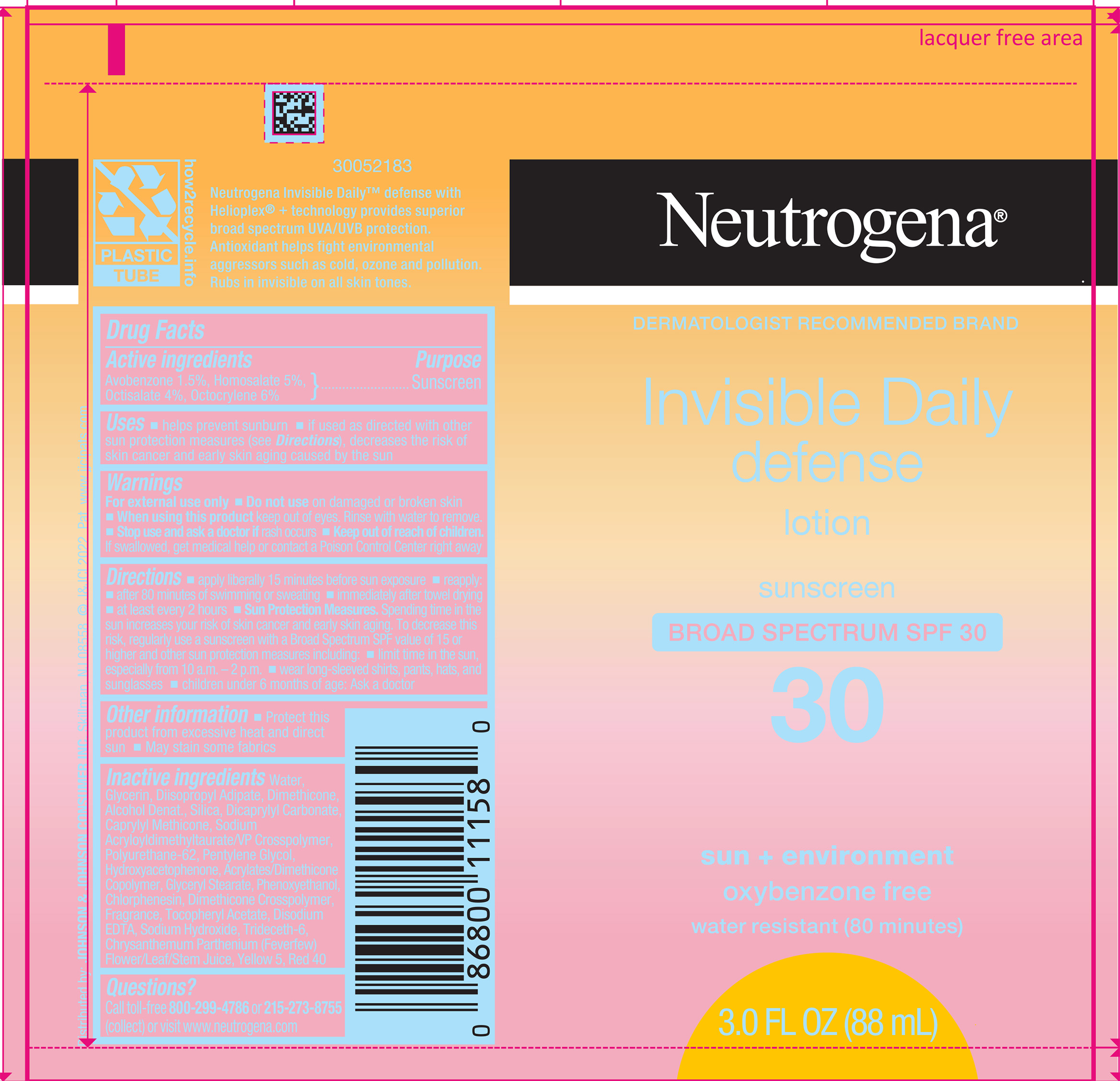 DRUG LABEL: Neutrogena Invisible Daily Defense Broad Spectrum SPF 30
NDC: 69968-0842 | Form: LOTION
Manufacturer: Kenvue Brands LLC
Category: otc | Type: HUMAN OTC DRUG LABEL
Date: 20251008

ACTIVE INGREDIENTS: AVOBENZONE 15 mg/1 mL; HOMOSALATE 50 mg/1 mL; OCTISALATE 40 mg/1 mL; OCTOCRYLENE 60 mg/1 mL
INACTIVE INGREDIENTS: DIISOPROPYL ADIPATE; WATER; DIMETHICONE; ALCOHOL; SILICON DIOXIDE; DICAPRYLYL CARBONATE; CAPRYLYL TRISILOXANE; PENTYLENE GLYCOL; GLYCERIN; HYDROXYACETOPHENONE; 2-ETHYLHEXYL ACRYLATE, METHACRYLATE, METHYL METHACRYLATE, OR BUTYL METHACRYLATE/HYDROXYPROPYL DIMETHICONE COPOLYMER (30000-300000 MW); GLYCERYL MONOSTEARATE; PHENOXYETHANOL; CHLORPHENESIN; DIMETHICONE CROSSPOLYMER (450000 MPA.S AT 12% IN CYCLOPENTASILOXANE); .ALPHA.-TOCOPHEROL ACETATE; EDETATE DISODIUM ANHYDROUS; SODIUM HYDROXIDE; TRIDECETH-6; FEVERFEW; FD&C YELLOW NO. 5; FD&C RED NO. 40; POLYURETHANE-62

Neutrogena Invisible Daily Defense Lotion Broad Spectrum SPF 30

Drug Facts

ACTIVE INGREDIENT

Active ingredients | Purpose
Avobenzone 1.5% | Sunscreen
Homosalate 5% | Sunscreen
Octisalate 4% | Sunscreen
Octocrylene 6% | Sunscreen

Uses

- helps prevent sunburn
- if used as directed with other sun protection measures (see Directions), decreases the risk of skin cancer and early skin aging caused by the sun

Warnings

For external use only

Do not use on damaged or broken skin

When using this product keep out of eyes. Rinse with water to remove.

Stop use and ask a doctor if rash occurs

Keep out of reach of children. If swallowed, get medical help or contact a Poison Control Center right away

Directions

- apply liberally 15 minutes before sun exposure
- reapply:
  - after 80 minutes of swimming or sweating
  - immediately after towel drying
  - at least every 2 hours
- Sun Protection Measures. Spending time in the sun increases your risk of skin cancer and early skin aging. To decrease this risk, regularly use a sunscreen with a Broad Spectrum SPF value of 15 or higher and other sun protection measures including:
  - limit time in the sun, especially from 10 a.m. – 2 p.m.
  - wear long-sleeved shirts, pants, hats, and sunglasses
- children under 6 months of age: Ask a doctor

Other information

- Protect this product from excessive heat and direct sun
- May stain some fabrics

Inactive ingredients

Water, Glycerin, Diisopropyl Adipate, Dimethicone, Alcohol Denat., Silica, Dicaprylyl Carbonate, Caprylyl Methicone, Sodium Acryloyldimethyltaurate/VP Crosspolymer, Polyurethane-62, Pentylene Glycol, Hydroxyacetophenone, Acrylates/Dimethicone Copolymer, Glyceryl Stearate, Phenoxyethanol, Chlorphenesin, Dimethicone Crosspolymer, Fragrance, Tocopheryl Acetate, Disodium EDTA, Sodium Hydroxide, Trideceth-6, Chrysanthemum Parthenium (Feverfew) Flower/Leaf/Stem Juice, Yellow 5, Red 40

Questions?

Call toll-free 800-299-4786 or 215-273-8755 (collect) or visit www.neutrogena.com

Distributed by: JOHNSON & JOHNSON CONSUMER INC. Skillman, NJ 08558

PRINCIPAL DISPLAY PANEL - 88 mL Tube Label

Neutrogena®

DERMATOLOGIST RECOMMENDED BRAND

Invisible Daily

defense

lotion

sunscreen

BROAD SPECTRUM SPF 30

30

sun + environment

oxybenzone free

water resistant (80 minutes)

3.0 FL OZ (88 mL)